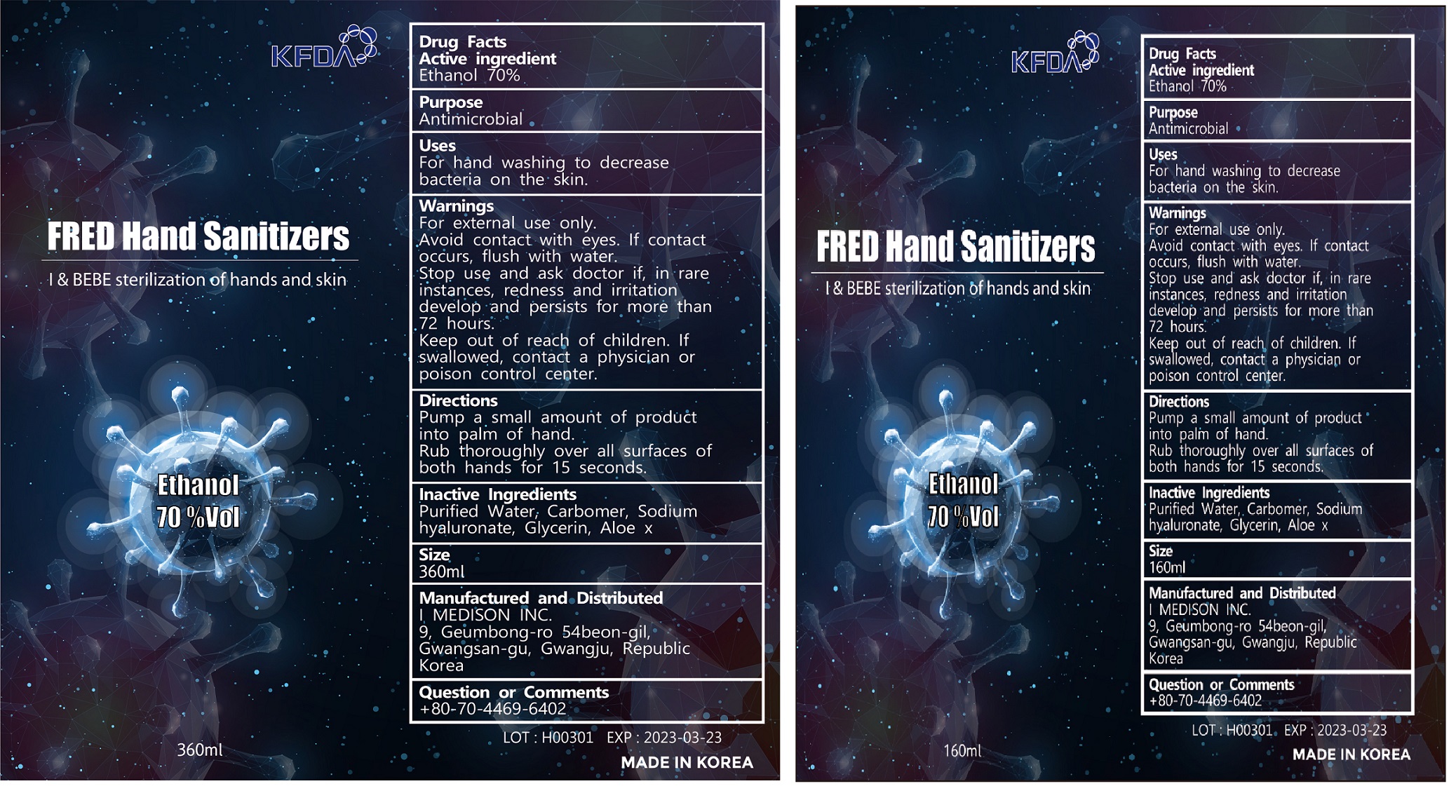 DRUG LABEL: I BEBE
NDC: 74650-0002 | Form: GEL
Manufacturer: I MEDISON CO., LTD.
Category: otc | Type: HUMAN OTC DRUG LABEL
Date: 20200413

ACTIVE INGREDIENTS: ALCOHOL 70 mL/100 mL
INACTIVE INGREDIENTS: ALOE VERA LEAF; HYALURONATE SODIUM; CARBOMER 940; WATER

Drug Facts

ACTIVE INGREDIENT

alcohol

INACTIVE INGREDIENT

Purified Water, Carbomer, sodium hyaluronate, glycerin, aloe X

PURPOSE

Antimicrobial

KEEP OUT OF REACH OF THE CHILDREN

WARNINGS

■ Flammable. Keep away from fire or flame.

■ For external use only.

■ Do not use in eyes.

■ lf swallowed, get medical help promptly.

■ Stop use, ask doctor lf irritation occurs.

■ Keep out of reach of children.

DOSAGE AND ADMINISTRATION

for external use only